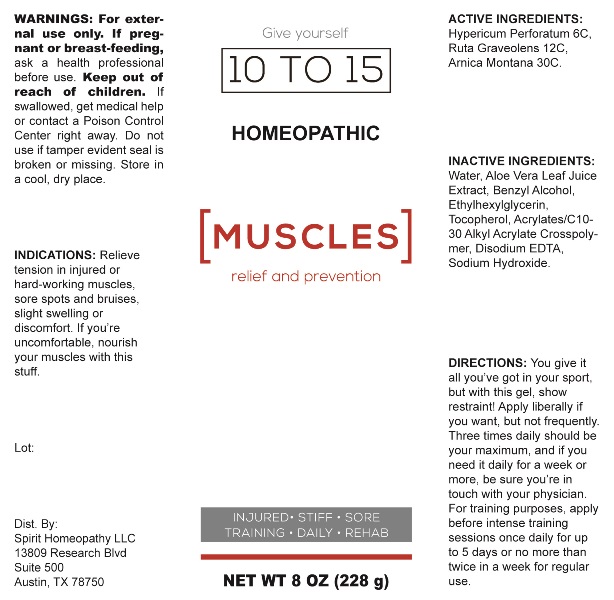 DRUG LABEL: Muscles
NDC: 73300-0002 | Form: GEL
Manufacturer: Spirit Homeopathy LLC
Category: homeopathic | Type: HUMAN OTC DRUG LABEL
Date: 20240122

ACTIVE INGREDIENTS: HYPERICUM PERFORATUM WHOLE 6 [hp_C]/1 g; RUTA GRAVEOLENS FLOWERING TOP 12 [hp_C]/1 g; ARNICA MONTANA WHOLE 30 [hp_C]/1 g
INACTIVE INGREDIENTS: WATER; CARBOMER INTERPOLYMER TYPE A (ALLYL SUCROSE CROSSLINKED); BENZYL ALCOHOL; ETHYLHEXYLGLYCERIN; TOCOPHEROL; SODIUM HYDROXIDE; ALOE VERA LEAF; EDETATE DISODIUM

Drug Facts:

ACTIVE INGREDIENTS:

Hypericum Perforatum 6C, Ruta Graveolens 12C, Arnica Montana 30C.

INDICATIONS:

Relieve tension in injured or hard-working muscles, sore spots and bruises, slight swelling or discomfort. If you're uncomfortable, nourish your muscles with this stuff.

WARNINGS:

For external use only. If pregnant or breast-feeding, ask a health professional before use.

Keep out of reach of children. If swallowed, get medical help or a Poison Control Center right away.

Do not use if tamper evident seal is broken or missing.

Store in a cool, dry place.

Keep out of reach of children. If swallowed, get medical help or contact a Poison Control Center right away.

DIRECTIONS:

You give it all you've got in your sport, but with this gel, show restraint! Apply liberally if you want, but not frequently. Three times daily should be your maximum, and if you need it daily for a week or more, be sure you're in touch with your physician. For training purposes, apply before intense training sessions once daily for up to 5 days or no more than twice in a week for regular use.

INDICATIONS:

Relieve tension in injured or hard-working muscles, sore spots and bruises, slight swelling or discomfort. If you're uncomfortable, nourish your muscles with this stuff.

INACTIVE INGREDIENTS:

Water, Aloe Vera Leaf Juice Extract, Benzyl Alcohol, Ethylhexylglycerin, Tocopherol, Acrylates/C10-30 Alkyl Acrylate Crosspolymer, Disodium EDTA, Sodium Hydroxide.

QUESTIONS:

Dist. By: Spirit Homeopathy LLC

13809 Research Blvd

Suite 500

Austin, TX 78750

PACKAGE LABEL DISPLAY:

Give yourself

10 TO 15

HOMEOPATHIC

[MUSCLES]

relief and prevention

INJURED • STIFF • SORE

TRAINING • DAILY • REHAB

NET WT 8 OZ (228 g)